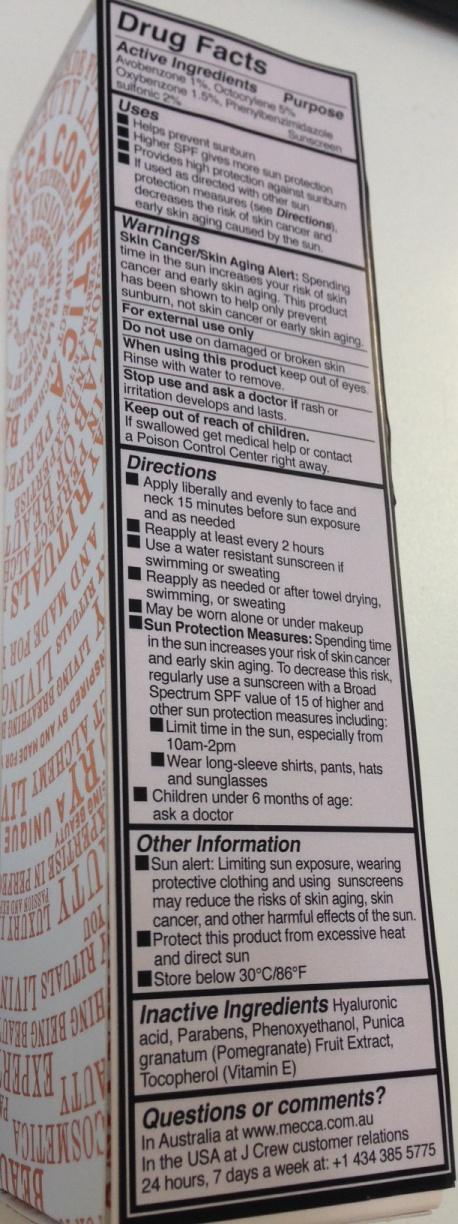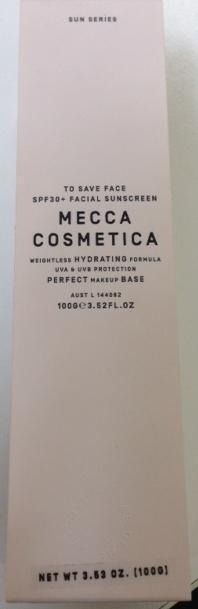 DRUG LABEL: To Save Face SPF 30 Plus
NDC: 69505-001 | Form: CREAM
Manufacturer: Mecca Brands Pty Ltd 
Category: otc | Type: HUMAN OTC DRUG LABEL
Date: 20141229

ACTIVE INGREDIENTS: AVOBENZONE 1 g/100 g; OXYBENZONE 1.5 g/100 g; ENSULIZOLE 2 g/100 g; OCTOCRYLENE 5 g/100 g
INACTIVE INGREDIENTS: HYALURONIC ACID; PHENOXYETHANOL; POMEGRANATE; TOCOPHEROL

Drug Facts

Active Ingredients

Avobenzone 1%, Octocrylene 5%, Oxybenzone 1.5%, Phenylbenzimidazole sulfonic 2%

Purpose

Sunscreen

Uses

- Helps prevent sunburn
- Higher SPF gives more sun protection
- If used as directed with other sun protection measures (see Directions), decreases the risk of skin cancer and early skin aging caused by the sun

Warnings

Skin Cancer/Skin Aging Alert: Spending time in the sun increases your risk of skin cancer and early skin aging. This product has been shown to help only prevent sunburn, not skin cancer or early skin aging.

For external use only

Do not use on damaged or broken skin

When using this product keep out of eyes. Rinse with water to remove.

Stop use and ask a doctor if rash or irritation develops and lasts.

Keep out of reach of children. If swallowed get medical help or contact a Poison Control Center right away.

Directions

- Apply liberally and evenly to face and neck 15 minutes before sun exposure and as needed
- Reapply at least every 2 hours
- Use a water resistant sunscreen if swimming or sweating
- Reapply as needed or after towel drying, swimming, or sweating
- May be worn alone or under makeup
- Sun Protection measures: Spending time in the sun increases your risk of skin cancer and early skin aging. To decrease this risk, regularly use a sunscreen with a Broad Spectrum SPF value of 15 or higher and other sun protection measures including:
-
  - Limit time in sun, especially from 10am-2pm
  - Wear long-sleeve shirts, pants, hats and sunglasses
- Children under 6 months of age: ask a doctor

Other Information

- Sun alert: Limiting sun exposure, wearing protective clothing and using sunscreens may reduce the risks of skin aging, skin cancer, and other harmful effects of the sun.
- Protect this product from excessive heat an direct sun
- Store below 30 degrees C/86 degrees F

Inactive Ingredients

Hyaluronic acid, Parabens, Phenoxyethanol, Punica granatum (Pomegranate) Fruit Extract, Tocopherol (Vitamin E)

Questions or comments?

In Australia at www.mecca.com.au

In the USA at J Crew customer relations 24 hours, 7 days a week at +1 434 385 5575

PACKAGE LABEL

SUN SERIES
TO SAVE FACE

SPF30+ FACIAL SUNSCREEN
MECCA COSMETICA

WEIGHTLESS HYDRATING FORMULA
UVA and UVB PROTECTION
PERFECT MAKEUP BASE

NET WT 3.53 OZ. (100G)